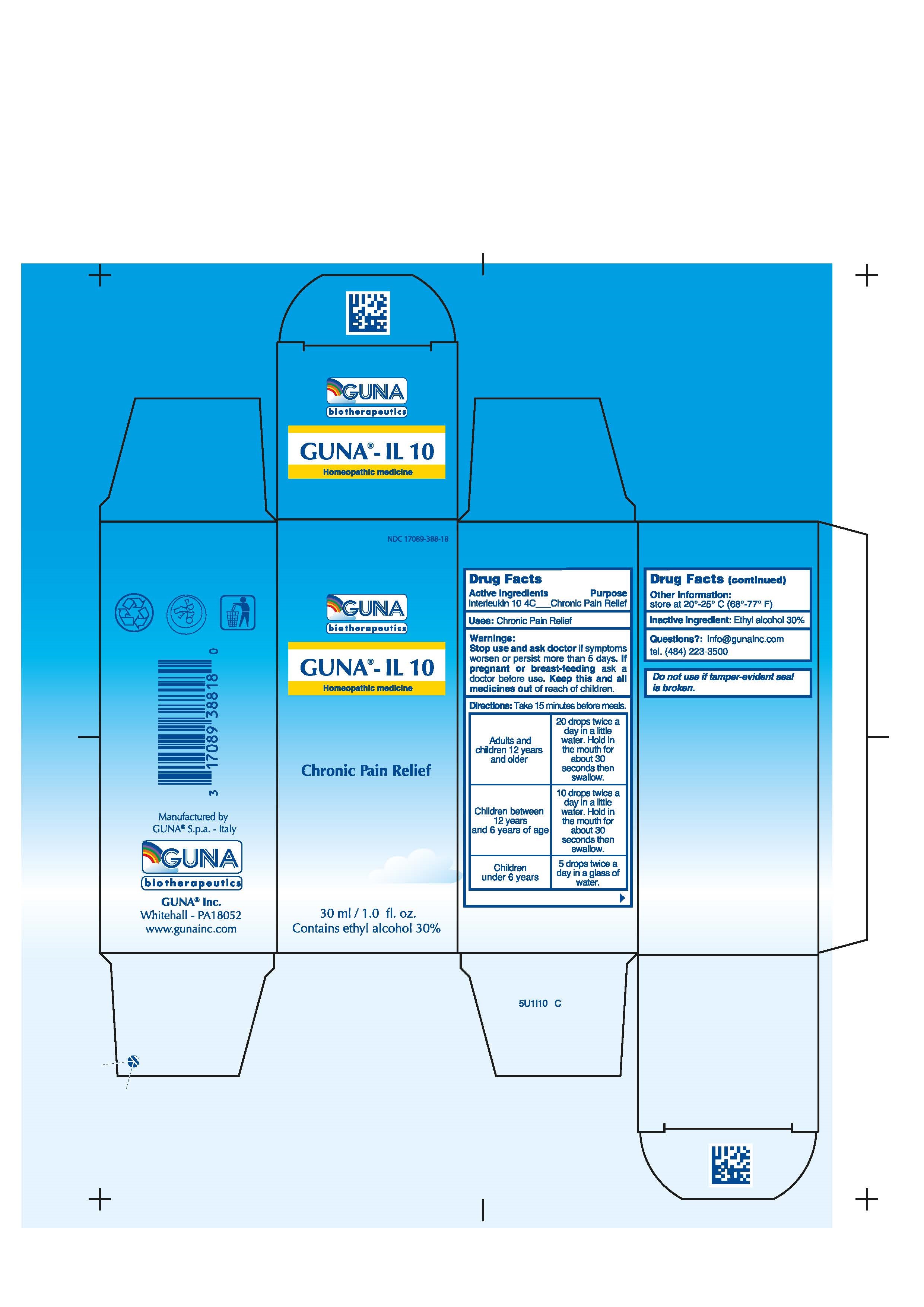 DRUG LABEL: GUNA-IL 10
NDC: 17089-388 | Form: SOLUTION/ DROPS
Manufacturer: Guna spa
Category: homeopathic | Type: HUMAN OTC DRUG LABEL
Date: 20221115

ACTIVE INGREDIENTS: INTERLEUKIN-10 4 [hp_C]/30 mL
INACTIVE INGREDIENTS: ALCOHOL 9 mL/30 mL

GUNA-IL 10

ACTIVE INGREDIENTS/PURPOSE

INTERLEUKIN-10 4C CHRONIC PAIN RELIEF

USES

CHRONIC PAIN RELIEF

WARNINGS

Stop use and ask doctor if symptoms worsen or persist more than 5 days.

If pregnant or breast-feeding ask a doctor professional before use.
Keep this and all medicines out of reach of children.
Contains ethyl alcohol 30%

PREGNANCY

If pregnant or breast-feeding ask a doctor before use.

WARNINGS

Keep this and all medicines out of reach of children.

DIRECTIONS

Adults and children 12 years and older 20 drops twice a day in a little water. Hold in the mouth for about 30 seconds then swallow.
Children between 12 years and 6 years of age 10 drops twice a day in a little water. Hold in the mouth for about 30 seconds then swallow.
Children under 6 years 5 drops twice a day in a glass of water.

QUESTIONS

Questions?: info@gunainc.com
Tel. (484) 223-3500

INDICATIONS AND USAGE

Directions: Take 15 minutes before meals.

Inactive ingredient: Ethyl alcohol 30%.